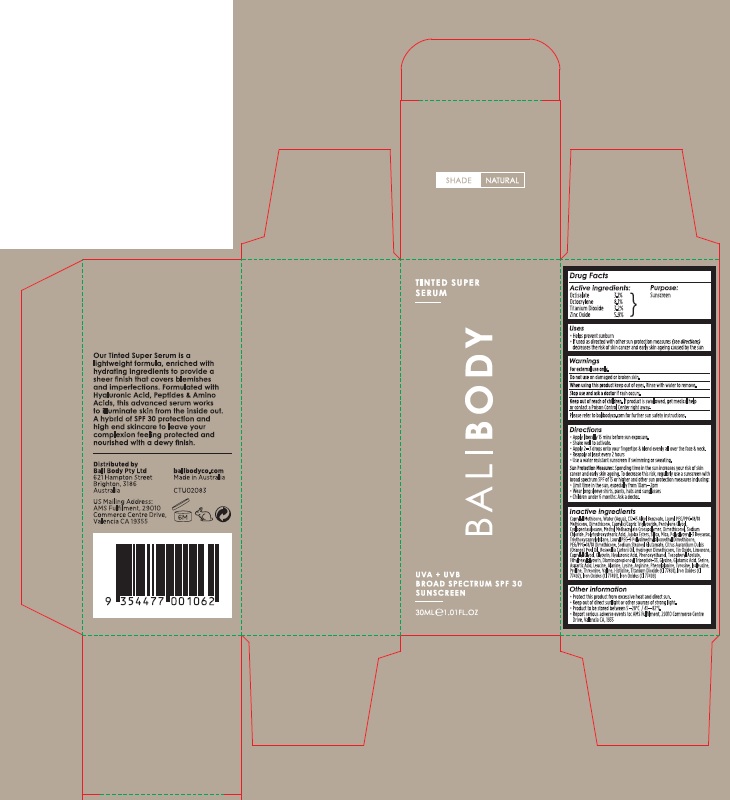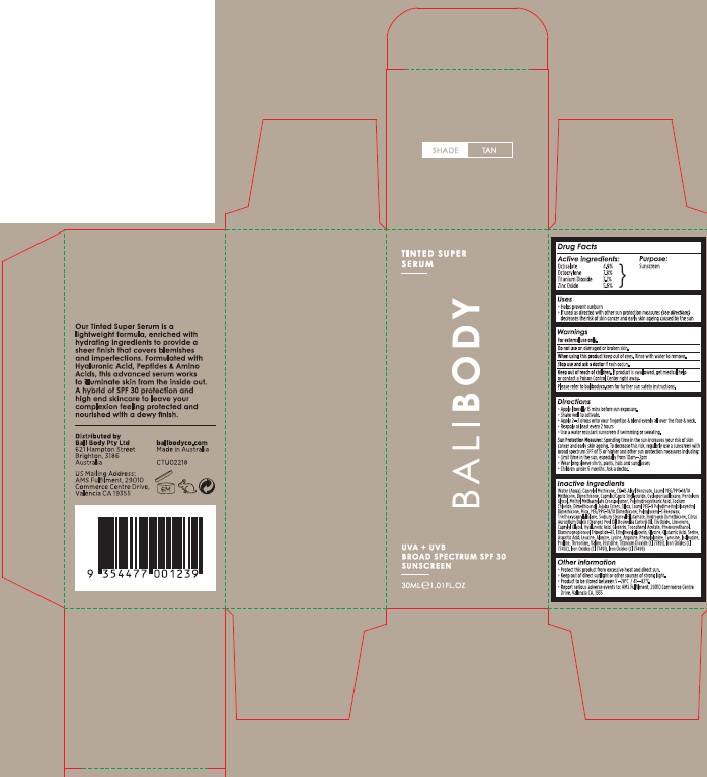 DRUG LABEL: Bali Body Tinted Super Serum Tan SPF 30
NDC: 70630-0032 | Form: LOTION
Manufacturer: Bali Body Pty Ltd
Category: otc | Type: HUMAN OTC DRUG LABEL
Date: 20241021

ACTIVE INGREDIENTS: OCTOCRYLENE 78 mg/1 mL; OCTISALATE 49 mg/1 mL; TITANIUM DIOXIDE 31 mg/1 mL; ZINC OXIDE 56 mg/1 mL
INACTIVE INGREDIENTS: DIMETHICONOL (2000 CST); SODIUM STEAROYL GLUTAMATE; ORANGE OIL; HYDROGEN DIMETHICONE (13 CST); .ALPHA.-TOCOPHEROL ACETATE; GLUTAMIC ACID; SODIUM CHLORIDE; POLYHYDROXYSTEARIC ACID (2300 MW); TRIETHOXYCAPRYLYLSILANE; ALKYL (C12-15) BENZOATE; LAURYL PEG/PPG-18/18 METHICONE; CYCLOMETHICONE 5; HYALURONIC ACID; SILICON DIOXIDE; ETHYLHEXYLGLYCERIN; ASPARTIC ACID; LEUCINE; LYSINE; PHENYLALANINE; JOJOBA OIL, RANDOMIZED; MICA; LAURYL PEG-9 POLYDIMETHYLSILOXYETHYL DIMETHICONE; PEG/PPG-18/18 DIMETHICONE; DIMETHICONE; MEDIUM-CHAIN TRIGLYCERIDES; PENTYLENE GLYCOL; FRANKINCENSE OIL; STANNOUS OXIDE; GLYCERIN; GLYCINE; FERRIC OXIDE YELLOW; CAPRYLYL TRISILOXANE; WATER; METHYL METHACRYLATE/GLYCOL DIMETHACRYLATE CROSSPOLYMER; FERRIC OXIDE RED; ALANINE; TYROSINE; PROLINE; ARGININE; ISOLEUCINE; THREONINE; VALINE; HISTIDINE; FERROSOFERRIC OXIDE; LIMONENE, (+)-; CAPRYLYL GLYCOL; PHENOXYETHANOL; SERINE

Bali Body Tinted Super Serum SPF 30

Active ingredients:- Natural Shade

Octisalate 3.1%

Octocrylene 8.1%

Titanium Dioxide 3.2%

Zinc Oxide 5.9%

Active ingredients - Tan Shade

Octisalate 4.9%

Octocrylene 7.8%

Titanium Dioxide 3.1%

Zinc Oxide 5.6%

Purpose

Sunscreen

Uses

- Helps prevent sunburn
- If used as directed with other sun protection measures (see directions) decreases the risk of skin cancer and early skin ageing caused by the sun

Warnings

For external use only.

Do not use

on damaged or broken skin.

When using this product

keep out of eyes. Rinse with water to remove.

Stop use and ask a doctor

if rash occurs.

Keep out of reach of children.

If product is swallowed, get medical help or contact a Poison Control Center right away.

Please refer to balibodyco.com for further sun safety instructions.

Directions

- Apply liberally 15 mins before sun exposure.
- Shake well to activate.
- Apply 2-3 drops onto your fingertips & blend evenly all over the face & neck.
- Reapply at least every 2 hours
- Use a water resistant sunscreen if swimming or sweating.

Sun Protection Measures: Spending time in the sun increases your risk of skin cancer and early skin ageing. To decrease this risk, regularly use a sunscreen with broad spectrum SPF of 15 or higher and other sun protection measures including:

- Limit time in the sun, especially from 10am - 2pm
- Wear long sleeve shirts, pants, hats and sunglasses
- Children under 6 months: Ask a doctor.

Inactive ingredients - Natural Shade

Caprylyl Methicone, Water (Aqua), C12-15 Alkyl Benzoate, Lauryl PEG/PPG-18/18 Methicone, Dimethicone, Caprylic/Capric Triglyceride, Pentylene Glycol, Cyclopentasiloxane, Methyl Methacrylate Crosspolymer, Dimethiconol, Sodium Chloride, Polyhydroxystearic Acid, Jojoba Esters, Silica, Mica, Polyglyceryl-3 Beeswax, Triethoxycaprylylsilane, Lauryl PEG-9 Polydimethylsiloxyethyl Dimethicone, PEG/PPG-18/18 Dimethicone, Sodium Stearoyl Glutamate, Citrus Aurantium Dulcis (Orange) Peel Oil, Boswellia Carterii Oil, Hydrogen Dimethicone, Tin Oxide, Limonene, Caprylyl Glycol, Glycerin, Hyaluronic Acid, Phenoxyethanol, Tocopheryl Acetate, Ethylhexylglycerin, Diaminopropionoyl Tripeptide-33, Glycine, Glutamic Acid, Serine, Aspartic Acid, Leucine, Alanine, Lysine, Arginine, Phenylalanine, Tyrosine, Isoleucine, Proline, Threonine, Valine, Histidine, Titanium Dioxide (CI 77891), Iron Oxides (CI 77492), Iron Oxides (CI 77491), Iron Oxides (CI 77499)

Inactive ingredients - Tan Shade

Water (Aqua), Caprylyl Methicone, C12-15 Alkyl Benzoate, Lauryl PEG/PPG-18/18 Methicone, Dimethicone, Caprylic/Capric Triglyceride, Cyclopentasiloxane, Pentylene Glycol, Methyl Methacrylate Crosspolymer, Polyhydroxystearic Acid, Sodium Chloride, Dimethiconol, Jojoba Esters, Silica, Lauryl PEG-9 Polydimethylsiloxyethyl Dimethicone, Mica, PEG/PPG-18/18 Dimethicone, Polyglyceryl-3 Beeswax, Triethoxycaprylylsilane, Sodium Stearoyl Glutamate, Hydrogen Dimethicone, Citrus Aurantium Dulcis (Orange) Peel Oil, Boswellia Carterii Oil, Tin Oxide, Limonene, Caprylyl Glycol, Hyaluronic Acid, Glycerin, Tocopheryl Acetate, Phenoxyethanol, Diaminopropionoyl Tripeptide-33, Ethylhexylglycerin, Glycine, Glutamic Acid, Serine, Aspartic Acid, Leucine, Alanine, Lysine, Arginine, Phenylalanine, Tyrosine, Isoleucine, Proline, Threonine, Valine, Histidine, Titanium Dioxide (CI 77891), Iron Oxides (CI 77492), Iron Oxides (CI 77491), Iron Oxides (CI 77499)

Other information

- Protect this product from excessive heat and direct sun.
- Keep out of direct sunlight or other sources of strong light.
- Product to be stored between 5-28C/41-82F.
- Report serious adverse events to: AMS Fulfillment, 29010 Commerce Centre Drive, Valencia CA, 1935